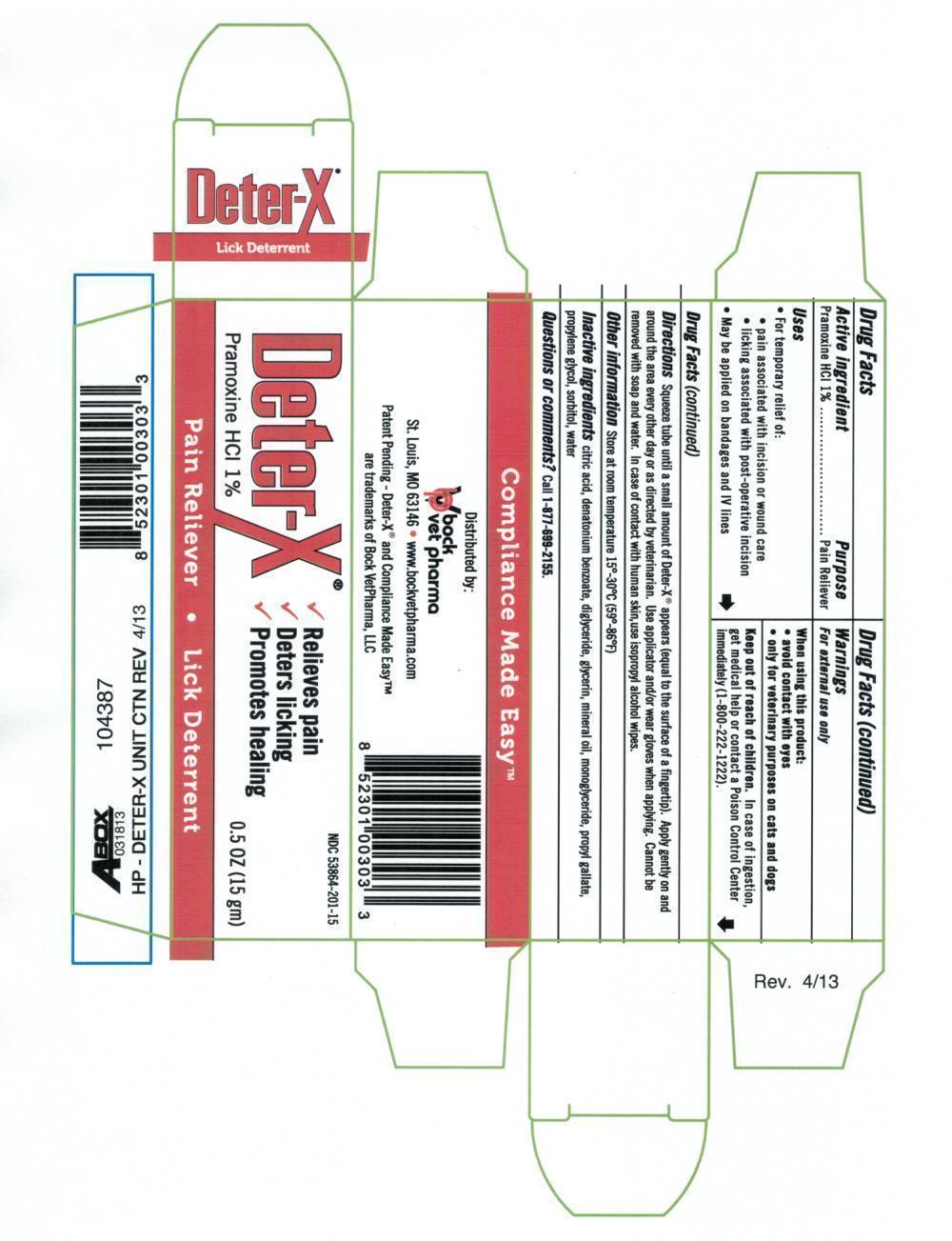 DRUG LABEL: Deter-X
NDC: 59228-601 | Form: OINTMENT
Manufacturer: EMS ACQUISITION CORP.
Category: animal | Type: OTC ANIMAL DRUG LABEL
Date: 20220422

ACTIVE INGREDIENTS: PRAMOXINE HYDROCHLORIDE 0.15 g/15 g
INACTIVE INGREDIENTS: ANHYDROUS CITRIC ACID; DENATONIUM BENZOATE; DIGLYCERIN; GLYCERIN; DIACETYLATED MONOGLYCERIDES; MINERAL OIL; PROPYL GALLATE; PROPYLENE GLYCOL; SORBITOL; WATER

EMS (as CMO) - Deter-X (59228-601)

ACTIVE INGREDIENT

PRAMOXINE HCL 1%